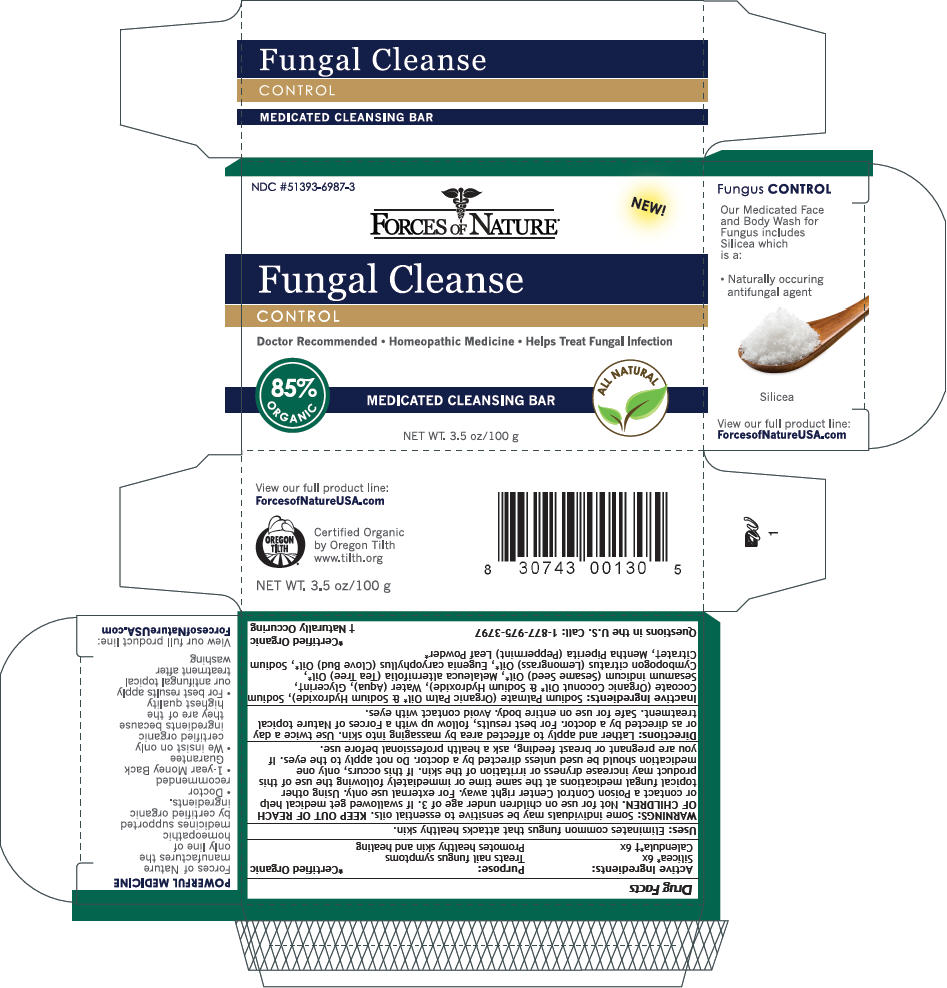 DRUG LABEL: FUNGAL CLEANSE
NDC: 51393-6987 | Form: SOAP
Manufacturer: Forces of Nature
Category: homeopathic | Type: HUMAN OTC DRUG LABEL
Date: 20131031

ACTIVE INGREDIENTS: CALENDULA OFFICINALIS FLOWERING TOP 6 [hp_X]/100 g; SILICON DIOXIDE 6 [hp_X]/100 g
INACTIVE INGREDIENTS: SESAME OIL; CLOVE OIL; TEA TREE OIL; WEST INDIAN LEMONGRASS OIL; SODIUM PALMATE; GLYCERIN; SODIUM COCOATE; SODIUM CITRATE; MENTHA PIPERITA LEAF; WATER

FUNGAL CLEANSE

Drug Facts

ACTIVE INGREDIENT

Active Ingredients: | Purpose:
Silicea [Certified Organic] 6x | Treats nail fungus symptoms
Calendula [Naturally Occuring] 6x | Promotes healthy skin and healing

Uses

Eliminates common fungus that attacks healthy skin.

WARNINGS

Some individuals may be sensitive to essential oils.

KEEP OUT OF REACH OF CHILDREN. Not for use on children under age of 3. If swallowed get medical help or contact a Poison Control Center right away.

For external use only.

Using other topical fungal medications at the same time or immediately following the use of this product may increase dryness or irritation of the skin. If this occurs, only one medication should be used unless directed by a doctor.

Do not apply to the eyes.

PREGNANCY OR BREAST FEEDING

If you are pregnant or breast feeding, ask a health professional before use.

Directions

Lather and apply to affected area by massaging into skin. Use twice a day or as directed by a doctor. For best results, follow up with a Forces of Nature topical treatment. Safe for use on entire body. Avoid contact with eyes.

Inactive Ingredients

Sodium Palmate (Organic Palm Oil [Certified Organic] & Sodium Hydroxide), Sodium Cocoate (Organic Coconut Oil & Sodium Hydroxide), Water (Aqua), Glycerin [Naturally Occuring] , Sesamum indicum (Sesame Seed) Oil, Melaleuca alternifolia (Tea Tree) Oil, Cymbopogon citratus (Lemongrass) Oil, Eugenia caryophyllus (Clove Bud) Oil, Sodium Citrate, Mentha Piperita (Peppermint) Leaf Powder

Questions in the U.S. Call

1-877-975-3797

PRINCIPAL DISPLAY PANEL - 100 g Box

NDC #51393-6987-3

FORCES OF NATURE®

NEW!

Fungal Cleanse

CONTROL

Doctor Recommended • Homeopathic Medicine • Helps Treat Fungal Infection

85%
ORGANIC

MEDICATED CLEANSING BAR

ALL NATURAL

NET WT. 3.5 oz/100 g